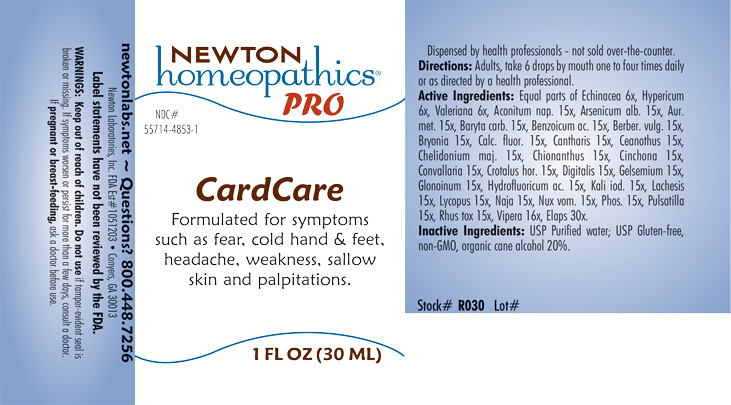 DRUG LABEL: CardCare
NDC: 55714-4853 | Form: LIQUID
Manufacturer: Newton Laboratories, Inc.
Category: homeopathic | Type: HUMAN OTC DRUG LABEL
Date: 20230925

ACTIVE INGREDIENTS: LYCOPUS VIRGINICUS 15 [hp_X]/1 mL; ANEMONE PULSATILLA 15 [hp_X]/1 mL; VIPERA BERUS VENOM 16 [hp_X]/1 mL; ECHINACEA, UNSPECIFIED 6 [hp_X]/1 mL; HYPERICUM PERFORATUM 6 [hp_X]/1 mL; ACONITUM NAPELLUS 15 [hp_X]/1 mL; BARIUM CARBONATE 15 [hp_X]/1 mL; VALERIAN 6 [hp_X]/1 mL; BRYONIA ALBA ROOT 15 [hp_X]/1 mL; ARSENIC TRIOXIDE 15 [hp_X]/1 mL; BENZOIC ACID 15 [hp_X]/1 mL; CHELIDONIUM MAJUS 15 [hp_X]/1 mL; HYDROFLUORIC ACID 15 [hp_X]/1 mL; POTASSIUM IODIDE 15 [hp_X]/1 mL; LACHESIS MUTA VENOM 15 [hp_X]/1 mL; STRYCHNOS NUX-VOMICA SEED 15 [hp_X]/1 mL; MICRURUS CORALLINUS VENOM 30 [hp_X]/1 mL; LYTTA VESICATORIA 15 [hp_X]/1 mL; CEANOTHUS AMERICANUS LEAF 15 [hp_X]/1 mL; CHIONANTHUS VIRGINICUS BARK 15 [hp_X]/1 mL; CONVALLARIA MAJALIS 15 [hp_X]/1 mL; DIGITALIS 15 [hp_X]/1 mL; NITROGLYCERIN 15 [hp_X]/1 mL; NAJA NAJA VENOM 15 [hp_X]/1 mL; CALCIUM FLUORIDE 15 [hp_X]/1 mL; GOLD 15 [hp_X]/1 mL; BERBERIS VULGARIS ROOT BARK 15 [hp_X]/1 mL; CINCHONA OFFICINALIS BARK 15 [hp_X]/1 mL; CROTALUS HORRIDUS HORRIDUS VENOM 15 [hp_X]/1 mL; GELSEMIUM SEMPERVIRENS ROOT 15 [hp_X]/1 mL; PHOSPHORUS 15 [hp_X]/1 mL; TOXICODENDRON PUBESCENS LEAF 15 [hp_X]/1 mL
INACTIVE INGREDIENTS: WATER; ALCOHOL

CardCare 4853L

INDICATIONS & USAGE SECTION

Formulated for symptoms such as fear, cold hands & feet, headache, weakness, sallow skin and palpitations.

DOSAGE & ADMINISTRATION SECTION

Directions: Adults, take 6 drops by mouth one to four times daily or as directed by a health professional.

OTC - ACTIVE INGREDIENT SECTION

Equal of Echinacea 6x, Hypericum 6x, Valeriana 6x, Aconitum nap. 15x, Arsenicum alb. 15x, Aur. met. 15x, Baryta carb. 15x, Benzoicum ac. 15x, Berber. vulg. 15x, Bryonia 15x, Calc. fluor. 15x, Cantharis 15x, Ceanothus 15x, Chelidonium maj. 15x, Chionanthus 15x, Cinchona 15x, Convallaria 15x, Crotalus hor. 15x, Digitalis 15x, Gelsemium 15x, Glonoinum 15x, Hydrofluoricum ac. 15x, Kali iod. 15x, Lachesis 15x, Lycopus 15x, Naja 15x, Nux vom. 15x, Phos. 15x, Pulsatilla 15x, Rhus tox. 15x, Vipera 16x, Elaps 30x.

OTC - PURPOSE SECTION

Formulated for symptoms such as fear, cold hands & feet, headache, weakness, sallow skin and palpitations.

INACTIVE INGREDIENT SECTION

Inactive Ingredients: USP Purified water; USP Gluten-free, non-GMO, organic cane alcohol 20%.

OTC - QUESTIONS SECTION

newtonlabs.net - Questions? 800.448.7256

Newton Laboratories, Inc. FDA Est # 1051203 Conyers, GA 30013

WARNINGS SECTION

WARNINGS: Keep out of reach of children. Do not use if tamper-evident seal is broken or missing. If symptoms worsen or persist for more than a few days, consult a doctor. If pregnant or breast-feeding, ask a doctor before use.

OTC - PREGNANCY OR BREAST FEEDING SECTION

If pregnant or breast-feeding, ask a doctor before use.

OTC - KEEP OUT OF REACH OF CHILDREN SECTION

Keep out of reach of children.